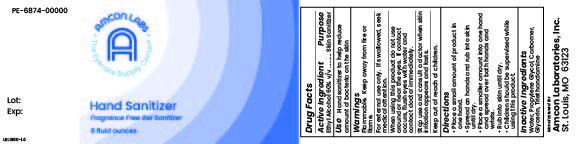 DRUG LABEL: Amcon Labs Hand Sanitizer Fragrance Free Gel Sanitizer
NDC: 51801-437 | Form: GEL
Manufacturer: Nomax, Inc.
Category: otc | Type: HUMAN OTC DRUG LABEL
Date: 20231120

ACTIVE INGREDIENTS: ALCOHOL 600 mL/1 L
INACTIVE INGREDIENTS: PROPYLENE GLYCOL; CARBOMER INTERPOLYMER TYPE A (ALLYL SUCROSE CROSSLINKED); WATER; GLYCERIN; TROLAMINE

Amcon Labs Hand Sanitizer Fragrance Free Gel Sanitizer

Active Ingredient

Ethyl Alcohol 60% v/v

Purpose

Skin Sanitizer

Use

Hand sanitizer to help reduce amount of bacteria on the skin

Warnings

Flammable. Keep away from fire or flame.

For external use only. If swallowed, seek medical attention.

When using this product do not use around or near the eyes. If contact occurs, flush eyes with water and contact doctor immediately.

Keep out of reach of children.

Directions

- Place a small amount of product in one hand.
- Spread on hands and run into skin until dry.
- Place a smaller amount into one hand and spread over both hands and wrists.
- Rub into skin until dry.
- Children should be supervised while using this product.

Inactive Ingredients

Water, Propylene Glycol, Carbomer, Glycerin, Triethanolamine